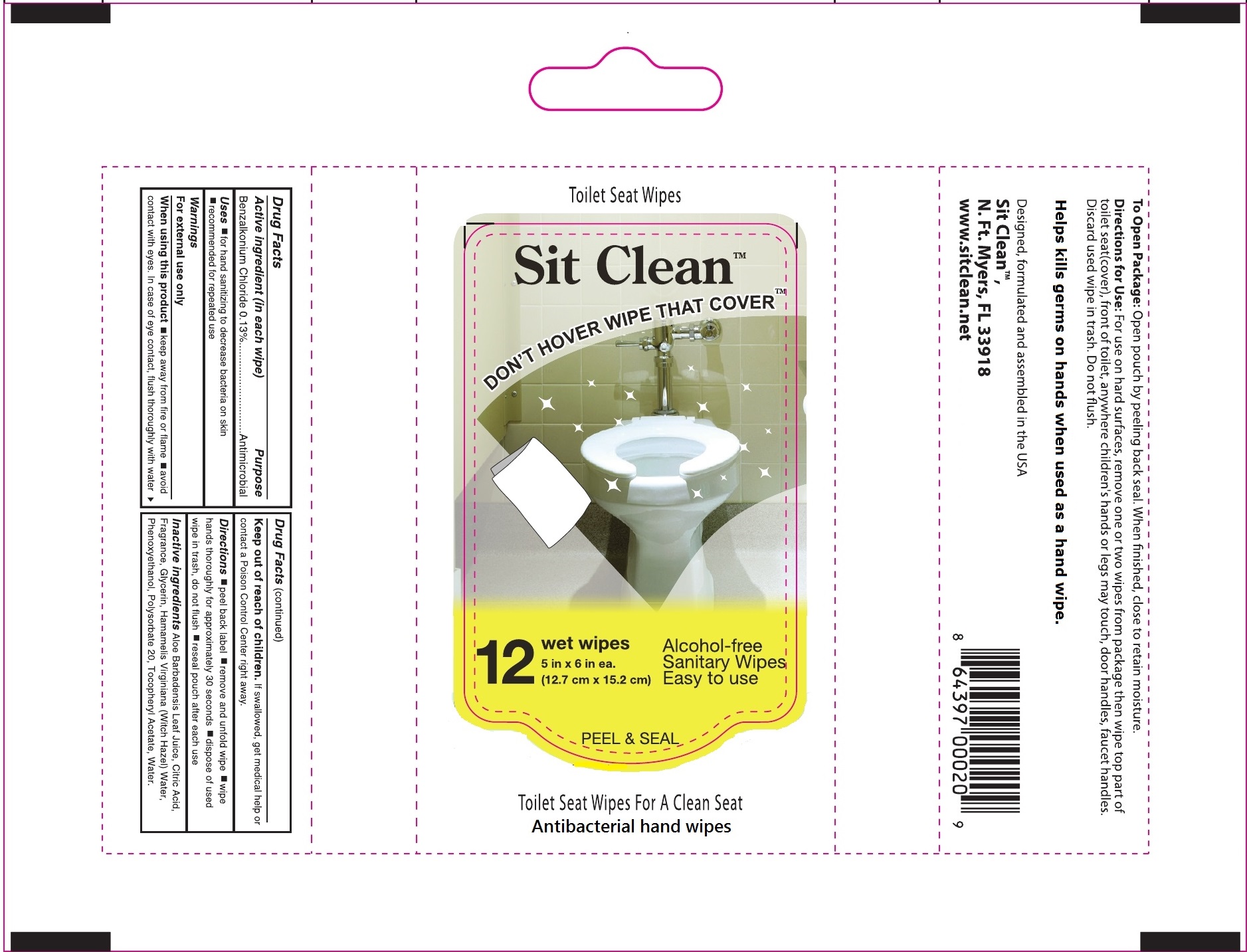 DRUG LABEL: Sit Clean
NDC: 70881-100 | Form: CLOTH
Manufacturer: Sit Clean
Category: otc | Type: HUMAN OTC DRUG LABEL
Date: 20160818

ACTIVE INGREDIENTS: BENZALKONIUM CHLORIDE .13 g/1 g
INACTIVE INGREDIENTS: ALOE VERA LEAF; CITRIC ACID ACETATE; GLYCERIN; HAMAMELIS VIRGINIANA LEAF; PHENOXYETHANOL; POLYSORBATE 20; ALPHA-TOCOPHEROL ACETATE

Uses

- For hand sanitizing to decrease bacteria on the skin when water and soap are not available.
- Recommended for repeated use

Active Ingredient

Benzalkonium Chloride .13%

Purpose

Antimicrobial

Warnings

- For external use only
- When using this product do not use in or near eyes. If contact occurs, flush thoroughly with water.

Keep out of reach of children

- If swallowed, get medical help or contact a Poison Control Center right away.

Inactive ingredeints

Aloe Barbadensis Leaf Juice, Citric Acid, Fragrance, Glycerin, Hamamelis, Virginiana (Witch Hazel) Bark/Leaf/Twig Extract, Phenoxyethanol, Polysorbate 20,Tocopheryl Acetate, Water

Dosage and Administration

- Peel back label
- Remove and unfold wipe
- Wipe hands thoroughly for approximately 30 seconds
- Dispose of used wipe in trash, do not flush
- Reseal pouch after each use

SPL UNCLASSIFIED SECTION

Designed, Formulated and assembled in the USA

Sit Clean TM

N. Ft. Myers, FL 33918

www.sitclean.net

Principal display panel

Sit Clean

Don't hover wipe that cover TM

Alcohol-free

Sanitary wipes

Easy to use

Toilet Seat Wipes

Antibacterial hand wipes

Helps kill germs on hands when used as a hand wipe